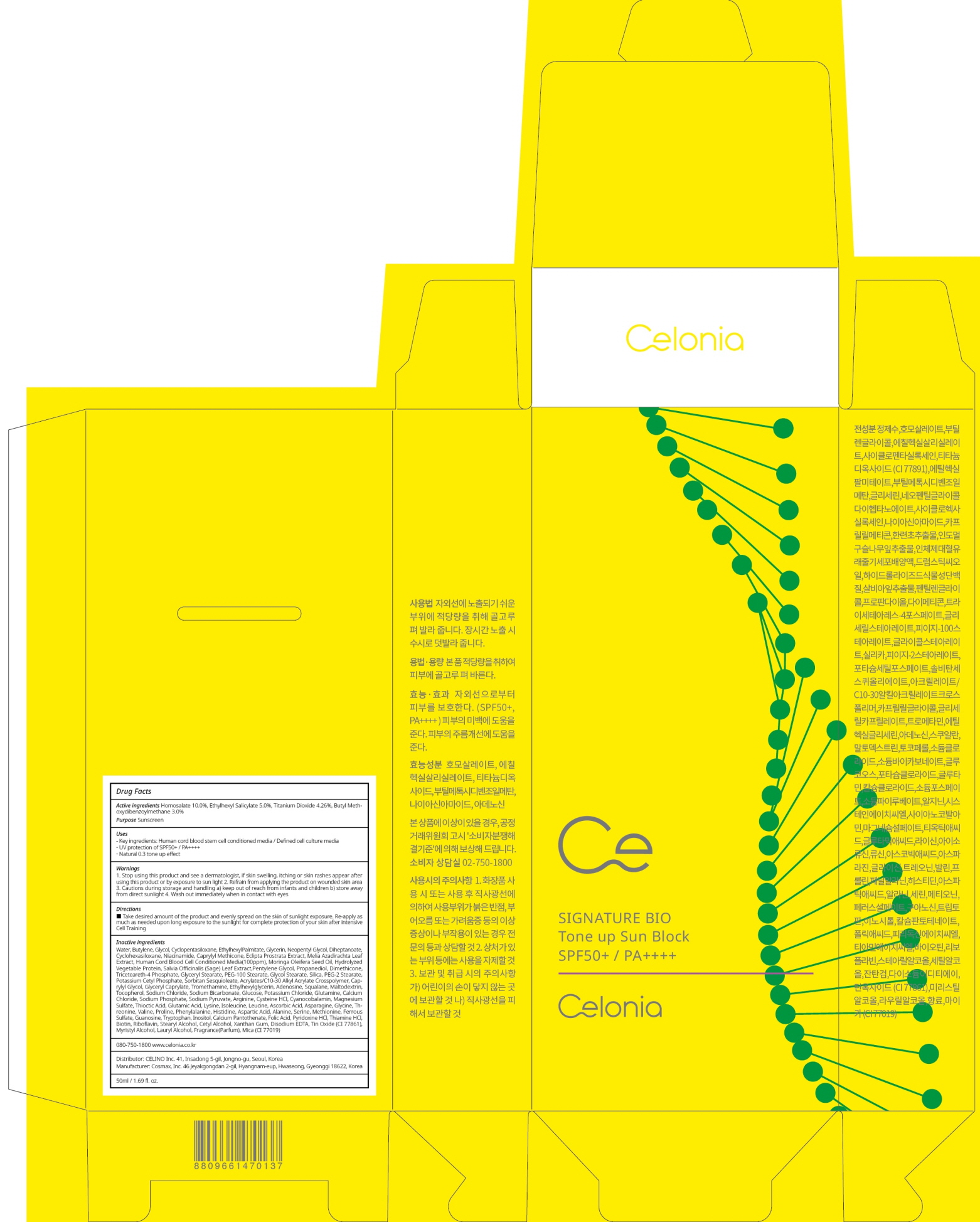 DRUG LABEL: CELONIA SIGNATURE BIO TONE UP SUN BLOCK
NDC: 73655-090 | Form: CREAM
Manufacturer: Celino Inc.
Category: otc | Type: HUMAN OTC DRUG LABEL
Date: 20200310

ACTIVE INGREDIENTS: Homosalate 5.00 g/50 mL; Octisalate 2.50 g/50 mL; Titanium Dioxide 2.13 g/50 mL; Avobenzone 1.50 g/50 mL
INACTIVE INGREDIENTS: Water; Butylene Glycol

ACTIVE INGREDIENT

Active ingredients: Homosalate 10.0%, Ethylhexyl Salicylate 5.0%, Titanium Dioxide 4.26%, Butyl Methoxydibenzoylmethane 3.0%

INACTIVE INGREDIENT

Inactive ingredients:

Water, Butylene Glycol,Cyclopentasiloxane,EthylhexylPalmitate,Glycerin,Neopentyl Glycol, Diheptanoate,Cyclohexasiloxane,Niacinamide,Caprylyl Methicone,Eclipta Prostrata Extract,Melia Azadirachta Leaf Extract,Human Cord Blood Cell Conditioned Media(100ppm),Moringa Oleifera Seed Oil,Hydrolyzed Vegetable Protein,Salvia Officinalis (Sage) Leaf Extract,Pentylene Glycol,Propanediol,Dimethicone,Triceteareth-4 Phosphate,Glyceryl Stearate,PEG-100 Stearate,Glycol Stearate,Silica,PEG-2 Stearate,Potassium Cetyl Phosphate,Sorbitan Sesquioleate,Acrylates/C10-30 Alkyl Acrylate Crosspolymer,Caprylyl Glycol,Glyceryl Caprylate,Tromethamine,Ethylhexylglycerin,Adenosine,Squalane,Maltodextrin,Tocopherol,Sodium Chloride,Sodium Bicarbonate,Glucose,Potassium Chloride,Glutamine,Calcium Chloride,Sodium Phosphate,Sodium Pyruvate,Arginine,Cysteine HCl,Cyanocobalamin,Magnesium Sulfate,Thioctic Acid,Glutamic Acid,Lysine,Isoleucine,Leucine,Ascorbic Acid,Asparagine,Glycine,Threonine,Valine,Proline,Phenylalanine,Histidine,Aspartic Acid,Alanine,Serine,Methionine,Ferrous Sulfate,Guanosine,Tryptophan,Inositol,Calcium Pantothenate,Folic Acid,Pyridoxine HCl,Thiamine HCl,Biotin,Riboflavin,Stearyl Alcohol,Cetyl Alcohol,Xanthan Gum,Disodium EDTA,Tin Oxide (CI 77861),Myristyl Alcohol,Lauryl Alcohol,Fragrance(Parfum),Mica (CI 77019)

PURPOSE

Purpose: Sunscreen

WARNINGS

1. Stop using this product and see a dermatologist, if skin swelling, itching or skin rashes appear after using this product or by exposure to sun light

2. Refrain from applying the product on wounded skin area

3. Cautions during storage and handling a) keep out of reach from infants and children b) store away from direct sunlight

4. Wash out immediately when in contact with eyes

QUESTIONS

080-750-1800

www.celonia.co.kr

DESCRIPTION

Uses:

Key ingredients: Human cord blood stem cell conditioned media / Defined cell culture media
UV protection of SPF50+ / PA++++
Natural 0.3 tone up effect

Directions:

Take desired amount of the product and evenly spread on the skin of sunlight exposure. Re-apply as much as needed upon long exposure to the sunlight for complete protection of your skin after intensive Cell Training